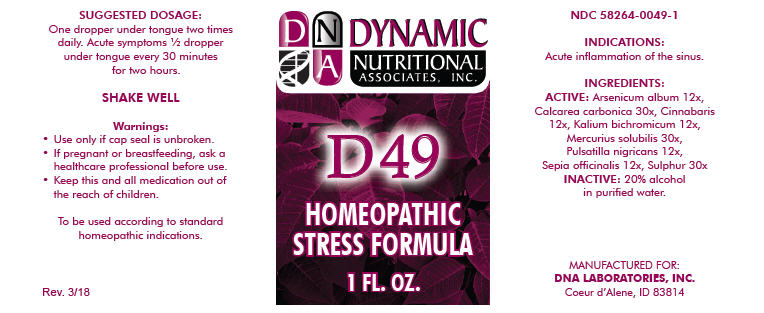 DRUG LABEL: D-49
NDC: 58264-0049 | Form: SOLUTION
Manufacturer: DNA Labs, Inc.
Category: homeopathic | Type: HUMAN OTC DRUG LABEL
Date: 20250113

ACTIVE INGREDIENTS: ARSENIC TRIOXIDE 12 [hp_X]/1 mL; OYSTER SHELL CALCIUM CARBONATE, CRUDE 30 [hp_X]/1 mL; MERCURIC SULFIDE 12 [hp_X]/1 mL; POTASSIUM DICHROMATE 12 [hp_X]/1 mL; MERCURIUS SOLUBILIS 30 [hp_X]/1 mL; ANEMONE PRATENSIS 12 [hp_X]/1 mL; SEPIA OFFICINALIS JUICE 12 [hp_X]/1 mL; SULFUR 30 [hp_X]/1 mL
INACTIVE INGREDIENTS: ALCOHOL; WATER

D-49

NDC 58264-0049-1

INDICATIONS

PURPOSE

Acute inflammation of the sinus.

INGREDIENTS

ACTIVE

Arsenicum album 12x, Calcarea carbonica 30x, Cinnabaris 12x, Kalium bichromicum 12x, Mercurius solubilis 30x, Pulsatilla nigricans 12x, Sepia officinalis 12x, Sulphur 30x

INACTIVE

20% alcohol in purified water.

SUGGESTED DOSAGE

One dropper under tongue two times daily. Acute symptoms ½ dropper under tongue every 30 minutes for two hours.

STORAGE AND HANDLING

SHAKE WELL

Warnings

- Use only if cap seal is unbroken.

PREGNANCY OR BREAST FEEDING

- If pregnant or breastfeeding, ask a healthcare professional before use.

KEEP OUT OF REACH OF CHILDREN

- Keep this and all medication out of the reach of children.

To be used according to standard homeopathic indications.

PRINCIPAL DISPLAY PANEL - 1 FL. OZ. Bottle Label

DYNAMIC
NUTRITIONAL
ASSOCIATES, INC.

D 49

HOMEOPATHIC
STRESS FORMULA

1 FL. OZ.